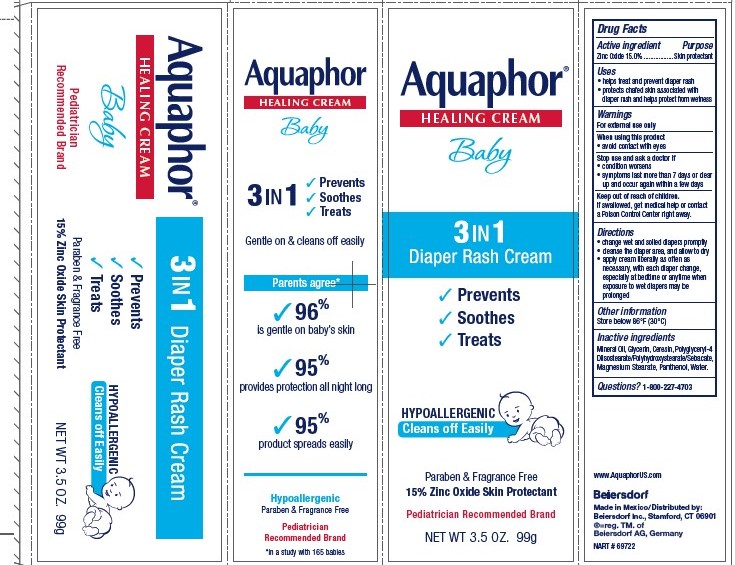 DRUG LABEL: Aquaphor Healing Diaper Rash
NDC: 10356-105 | Form: CREAM
Manufacturer: Beiersdorf Inc
Category: otc | Type: HUMAN OTC DRUG LABEL
Date: 20251215

ACTIVE INGREDIENTS: ZINC OXIDE 15 g/100 g
INACTIVE INGREDIENTS: MINERAL OIL; CERESIN; GLYCERIN; PANTHENOL; MAGNESIUM STEARATE; WATER; POLYGLYCERYL-4 ISOSTEARATE

Aquaphor Healing Diaper Rash Cream

ACTIVE INGREDIENT

Zinc Oxide 15%

PURPOSE

Skin Protectant

Uses
• helps treat and prevent diaper rash
• protects chafed skin associated with diaper rash and helps protect from wetness

WARNINGS

For external use only

When using this product • avoid contact with eyes

Stop use and ask a doctor if • condition worsens
• symptoms last more than 7 days or clear up and occur
again within a few days

Keep out of reach of children. If swallowed, get medical help
or contact a Poison Control Center right away.

Inactive Ingredients

Mineral Oil, Glycerin, Ceresin, Polyglyceryl-4 Diisostearate/Polyhydroxystearate/Sebacate,

Magnesium Stearate, Panthenol, Water

Questions or comments

1-800-227-4703

PACKAGE LABEL

Aquaphor Healing Cream

Baby

3 in 1

Diaper Rash Cream

Prevents Soothes Treats

Hypoallergenic

Cleans Off Easily

Paraben and Fragrance Free

15% Zinc Oxide Skin Protectant

Pediatrician Recommended Brand